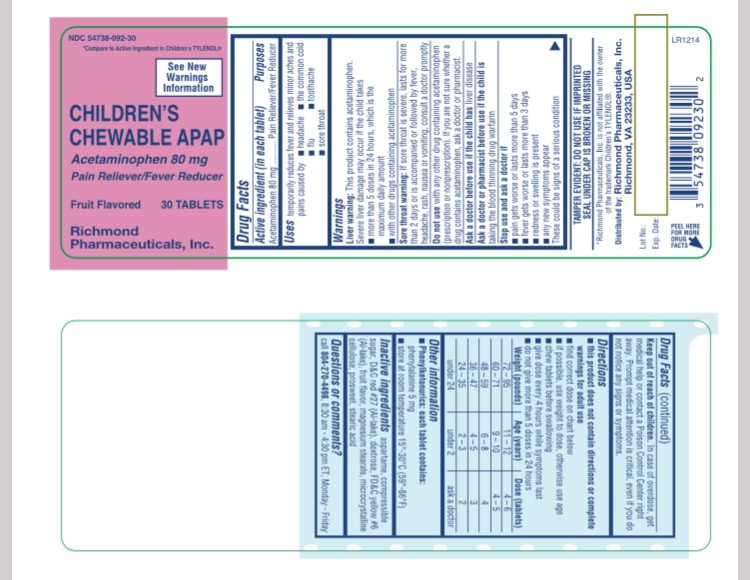 DRUG LABEL: Chewable Acetaminophen
NDC: 54738-092 | Form: TABLET, CHEWABLE
Manufacturer: Richmond Pharmaceuticals, Inc.
Category: otc | Type: HUMAN OTC DRUG LABEL
Date: 20171030

ACTIVE INGREDIENTS: ACETAMINOPHEN 80 mg/1 1
INACTIVE INGREDIENTS: ASPARTAME; INVERT SUGAR; D&C RED NO. 27; DEXTROSE; FD&C YELLOW NO. 6; MAGNESIUM STEARATE; MICROCRYSTALLINE CELLULOSE; STEARIC ACID

APAP Children Chewable Tablets, 80 mg

Active ingredient (in each tablet)

Acetaminophen 80 mg

Purpose

Pain reliever/fever reducer

Uses

- temporarily relieves minor aches and pains due to:
- headache
- sore throat
- flu
- toothache
- the common cold
- temporarily reduces fever

Warnings

Liver warning: This product contains acetaminophen. Severe liver damage may occur if your child takes:

- more than 5 doses in 24 hours, which is the maximum daily amount
- with other drugs containing acetaminophen

Allergy alert: Acetaminophen may cause severe skin reactions. Symptoms may include:

- skin reddening
- blisters
- rash

If a skin reaction occurs, stop use and seek medical help right away.

Sore throat warning: If sore throat is severe, persists for more than 2 days, is accompanied or followed by fever, headache, rash, nausea, or vomiting, consult a doctor promptly.

Do not use

- with any other drug containing acetaminophen (prescription or nonprescription). If you are not sure whether a drug contains acetaminophen, ask a doctor or pharmacist.
- if your child is allergic to acetaminophen or any of the inactive ingredients in this product

Ask a doctor before use if your child has

liver disease.

Ask a doctor or pharmacist before use if your child is

taking the blood thinning drug warfarin.

When using this product

do not exceed recommended dosage.

Stop use and ask a doctor if

- pain gets worse or lasts more than 5 days
- fever gets worse or lasts more than 3 days
- new symptoms occur
- redness or swelling is present

These could be signs of a serious condition.

Keep out of reach of children.

In case of accidental overdose, get medical help or contact a Poison Control Center (1-800-222-1222) right away. Prompt medical attention is critical for adults as well as for children even if you do not notice any signs or symptoms.

Directions

- this product does not contain directions or complete warnings for adult use
- do not give more than directed
- find the right dose on chart below. If possible, use weight to dose; otherwise, use age.
- chew before swallowing; this product will soften in mouth for ease of chewing
- repeat dose every 4 hours while symptoms last
- do not give more than 5 times in 24 hours
- do not give for more than 5 days unless directed by a doctor

Weight (lb) | Age (yr) | Dose (tablets)*
Under 24 | Under 2 | Ask a doctor
24-35 | 2-3 | 2
36-47 | 4-5 | 3
48-59 | 6-8 | 4
60-71 | 9-10 | 4-5
72-95 | 11-12 | 4-6

*or as directed by a doctor

Other information

- store at 25°C (77°F); excursions permitted between 15°-30°C (59°-86°F)
- avoid high humidity
- Phenylketonurics:each tablet contains: phenylalanine 5mg

Inactive ingredients

aspartame, compressible sugar, D&C red #27(Al lake), dextorse, FD&C yellow #6(Al lake), fruit flavor, magnesium stearate, microcrystaline cellulose, prosweet, stearice acid

Questions or comments?

TAMPER EVIDENT: DO NOT USE IF IMPRINTED SAFETY SEAL UNDER CAP IS BROKEN OR MISSING
call 804-270-4498, 8.30 am-4.30 pm ET, Monday - Friday

Principal display panel

NDC- 54738-092-30 - APAP 80MG CHEWABLE- 30 TABS